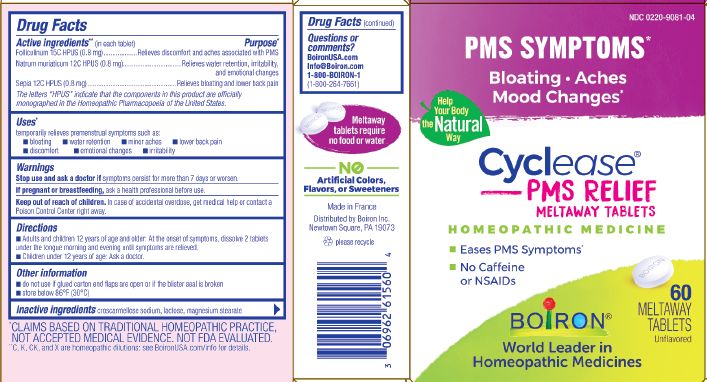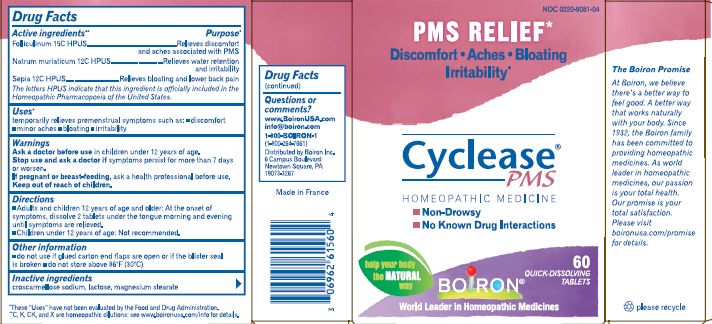 DRUG LABEL: Cyclease PMS
NDC: 0220-9081 | Form: TABLET
Manufacturer: Laboratoires Boiron
Category: homeopathic | Type: HUMAN OTC DRUG LABEL
Date: 20230530

ACTIVE INGREDIENTS: ESTRONE 15 [hp_C]/1 1; SODIUM CHLORIDE 12 [hp_C]/1 1; SEPIA OFFICINALIS JUICE 12 [hp_C]/1 1
INACTIVE INGREDIENTS: CROSCARMELLOSE SODIUM; LACTOSE; MAGNESIUM STEARATE

Cyclease PMS

ACTIVE INGREDIENT

Folliculinum 15C HPUS (0.8mg), Natrum muriaticum 12C HPUS (0.8mg), Sepia 12C HPUS (0.8mg)

INDICATIONS AND USAGE

Temporary relieves premenstrual symptoms such as: bloating, water retention, minor aches, lower back pain, discomfort, emotional changes, irritability

Do not use if glued carton end flaps are open or if the blister seal is broken

DOSAGE AND ADMINISTRATION

Adults and children 12 years of age and older: Dissolve 2 tablets in the mouth morning and evening until symptoms are relieved.
Children under 12 years of age: Not recommended

INACTIVE INGREDIENT

Croscarmellose sodium, lactose, magnesium stearate

HOW SUPPLIED

60 meltaway tablets

PURPOSE

Folliculinum 15C ...Relieves discomfort and aches associated with PMS
Natrum muriaticum 12C ...Relieves water retention and irritability
Sepia 12C...Relieves bloating and lower back pain.

STORAGE AND HANDLING

Store at 68-77o F (30oC)

Questions, Comments
Boironusa.com
info@boironusa.com
1-800-BOIRON-1
(1-800-264-7661)
Distributed by Boiron, Inc.

Newtown Square, PA 19073

Stop use and ask a doctor if symptoms persist for more than 7 days or worsen.

Keep out of reach of children
In case of accidental overdose, get medical help or contact a Poison Control Center right away.

PREGNANCY OR BREAST FEEDING

If pregnant or breast-feeding, ask a health professional before use.

DRUG INTERACTIONS

Safe - no side effects - no drug interactions - works naturally with your body

WARNINGS

Enter section text here

The letters "HPUS" indicate that the components in this product are officially monographed in the Homeopathic Pharmacopoeia of the United States.

*CLAIMS BASED ON TRADITIONAL HOMEOPATHIC PRACTICE NOT ACCEPTED MEDICAL EVIDENCE. NOT FDA EVALUATED.
**C,K,CK, and X are homeopathic dilutions: see BoironUSA.com/info for details.